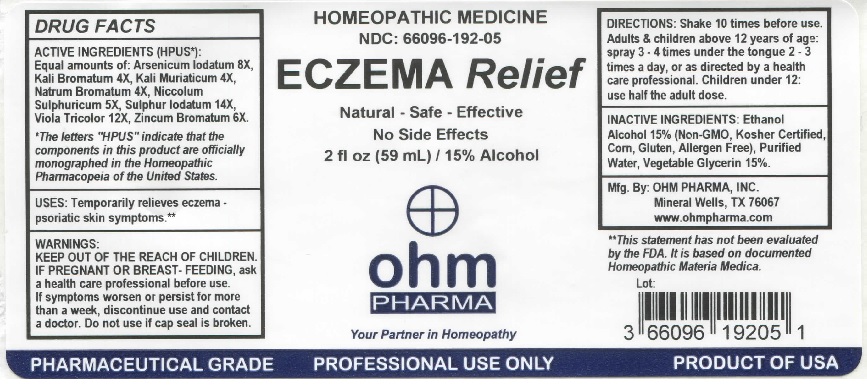 DRUG LABEL: Eczema Relief
NDC: 66096-192 | Form: LIQUID
Manufacturer: OHM PHARMA INC.
Category: homeopathic | Type: HUMAN OTC DRUG LABEL
Date: 20211229

ACTIVE INGREDIENTS: ARSENIC TRIIODIDE 8 [hp_X]/59 mL; POTASSIUM BROMIDE 4 [hp_X]/59 mL; POTASSIUM CHLORIDE 4 [hp_X]/59 mL; SODIUM BROMIDE 4 [hp_X]/59 mL; NICKEL SULFATE HEXAHYDRATE 5 [hp_X]/59 mL; SULFUR IODIDE 14 [hp_X]/59 mL; VIOLA TRICOLOR 12 [hp_X]/59 mL; ZINC BROMIDE 6 [hp_X]/59 mL
INACTIVE INGREDIENTS: ALCOHOL; WATER; GLYCERIN

OHM Eczema Relief

ACTIVE INGREDIENT

ACTIVE INGREDIENTS (HPUS*): Equal amounts of : Arsenicum Iodatum 8X, Kali Bromatum 4X, Kali Muriaticum 4X, Natrum Bromatum 4X, Niccolum Sulphuricum 5X, Sulphur Iodatum 14X, Viola Tricolor 12X, Zincum Bromatum 6X.

* The letters "HPUS" indicate that the components in this product are officially monographed in the Homeopathic Pharmacopeia of the United States.

INDICATIONS AND USAGE

USES: Temporarily relieves eczema - psoriatic skin symptoms.**

**This statement has not been evaluated by the FDA. It is based on documented Homeopathic Materia Medica.

WARNINGS

WARNINGS: IF PREGNANT OR BREAST-FEEDING, ask a health care professional before use. If symptoms worsen or persist for more than a week, discontinue use and contact a doctor.

- KEEP OUT OF REACH OF CHILDREN.

DOSAGE AND ADMINISTRATION

DIRECTIONS: Shake 10 times before use. Adults & children above 12 years of age: spray 3-4 times under the tongue 2-3 times a day, or as directed by a health care professional. Children under 12: use half the adult dose.

Do not use if cap seal is broken.

INACTIVE INGREDIENT

INACTIVE INGREDIENTS: Ethanol Alcohol 15% (Non-GMO, Kosher Certified, Corn, Gluten, Allergen Free), Purified Water, Vegetable Glycerin 15%.

QUESTIONS

Mfg. By: OHM PHARMA, INC. Mineral Wells, TX 76067

www.ohmpharma.com

PACKAGE LABEL

HOMEOPATHIC MEDICINE

NDC: 66096-192-05

ECZEMA Relief

Natural - Safe - Effective

No Side Effects

2 fl oz (59 mL) / 15% Alcohol

PRODUCT OF USA

PURPOSE

Temporarily relieves eczema.